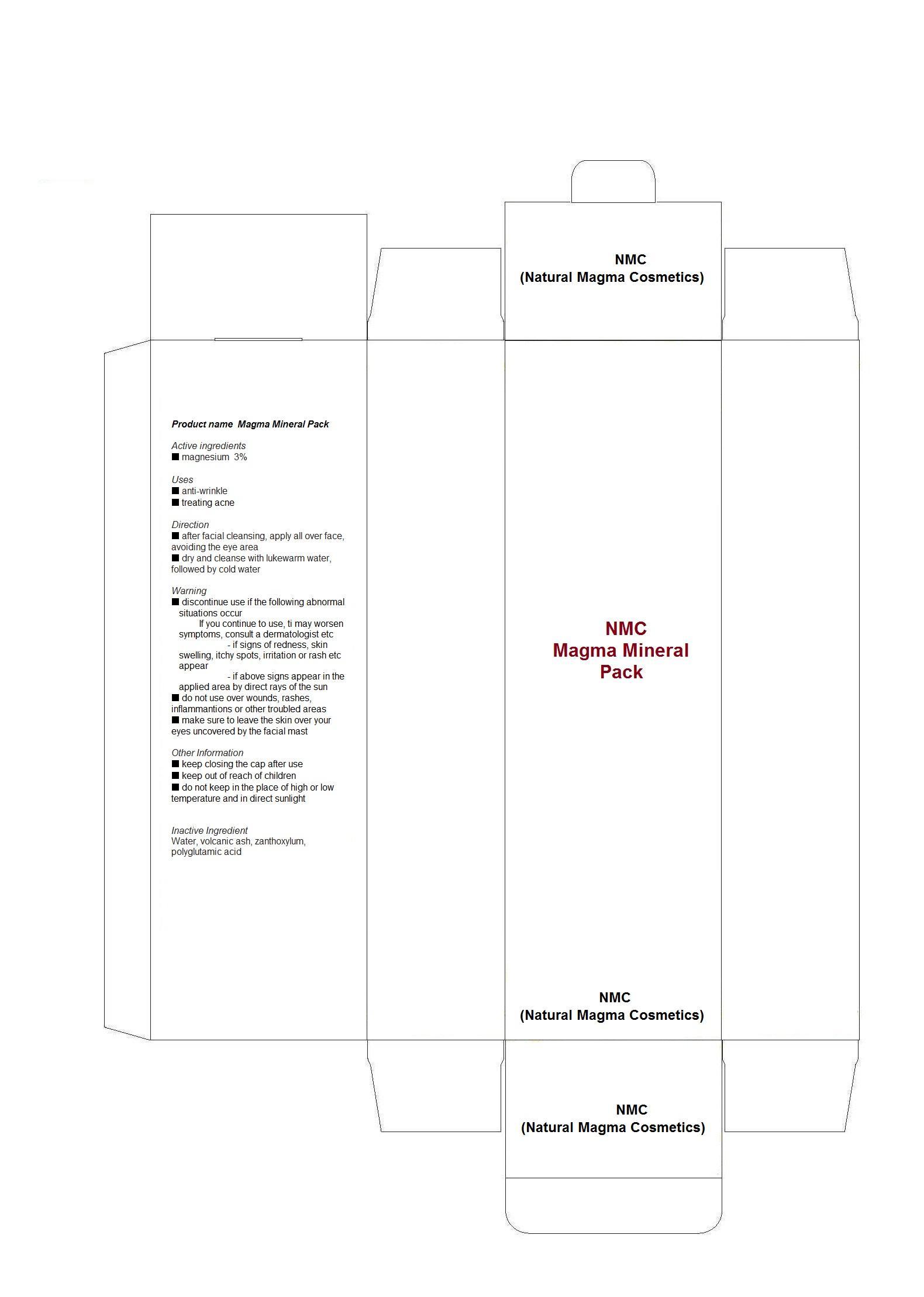 DRUG LABEL: NMC Magma Mineral Pack
NDC: 59220-1001 | Form: PLASTER
Manufacturer: NMC (Natural Magma Cosmetics)
Category: otc | Type: HUMAN OTC DRUG LABEL
Date: 20130708

ACTIVE INGREDIENTS: MAGNESIUM 3 g/100 g
INACTIVE INGREDIENTS: WATER; ZANTHOXYLUM ARMATUM VAR. ARMATUM FRUIT

Drug Facts

ACTIVE INGREDIENT

magnesium

INACTIVE INGREDIENT

water volcanic ash, zanthoxylum, polyglutamic acid

PURPOSE

anti-wrinkle, treating acne

keep out or reach of the children

INDICATIONS AND USAGE

after facial cleansing, apply all over face, avoiding the eye area
dry and cleanse with lukewarm water, followed by cold water

WARNINGS

be careful with the consumption for the one who is sensitive to estrogenic hormones

DOSAGE AND ADMINISTRATION

for topical use only